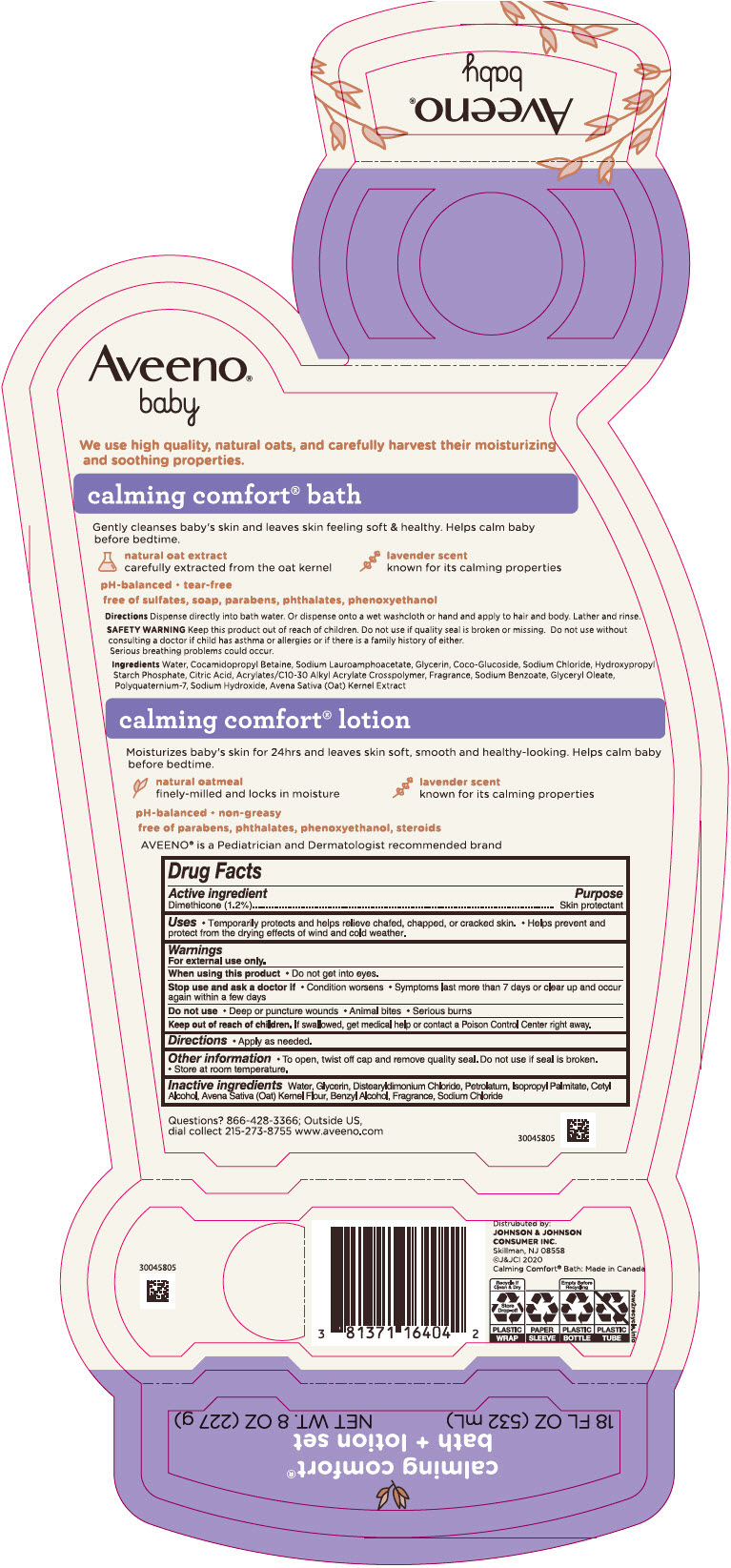 DRUG LABEL: Aveeno Baby Calming Comfort Bath Plus Set
NDC: 69968-0631 | Form: KIT | Route: TOPICAL
Manufacturer: Kenvue Brands LLC
Category: otc | Type: HUMAN OTC DRUG LABEL
Date: 20241106

ACTIVE INGREDIENTS: DIMETHICONE 12 mg/1 g
INACTIVE INGREDIENTS: BENZYL ALCOHOL; SODIUM CHLORIDE; WATER; GLYCERIN; DISTEARYLDIMONIUM CHLORIDE; PETROLATUM; ISOPROPYL PALMITATE; CETYL ALCOHOL; OATMEAL

Aveeno® baby calming comfort® bath plus lotion set
Aveeno baby calming comfort® lotion

Drug Facts

Active ingredient

Dimethicone 1.2%

Purpose

Skin protectant

Uses

- Temporarily protects and helps relieve chafed, chapped, or cracked skin
- Helps prevent and protect from the drying effects of wind and cold weather.

Warnings

For external use only.

When using this product

- Do not get into eyes.

Stop use and ask a doctor if

- Condition worsens
- Symptoms last more than 7 days or clear up and occur again within a few days.

Do not use on

- Deep or puncture wounds
- Animal bites
- Serious burns

Keep out of reach of children. If swallowed, get medical help or contact a Poison Control Center right away.

Directions

- Apply as needed.

Other information

- To open, twist off cap and remove quality seal. Do not use if seal is broken.
- Store at room temperature.

Inactive ingredients

Water , Glycerin, Distearyldimonium Chloride ,Petrolatum, Isopropyl Palmitate, Cetyl Alcohol, Avena Sativa (Oat) Kernel Flour, Benzyl Alcohol, Fragrance, Sodium Chloride

Questions?

866-428-3366; Outside US, dial collect 215-273-8755 www.aveeno.com

Distributed by:
JOHNSON & JOHNSON
CONSUMER INC.
Skillman, NJ 08558

PRINCIPAL DISPLAY PANEL - Kit Packet

Aveeno®
baby
calming comfort®
bath + lotion set

18 FL OZ (532 mL)

NET WT. 8 OZ (227 g)